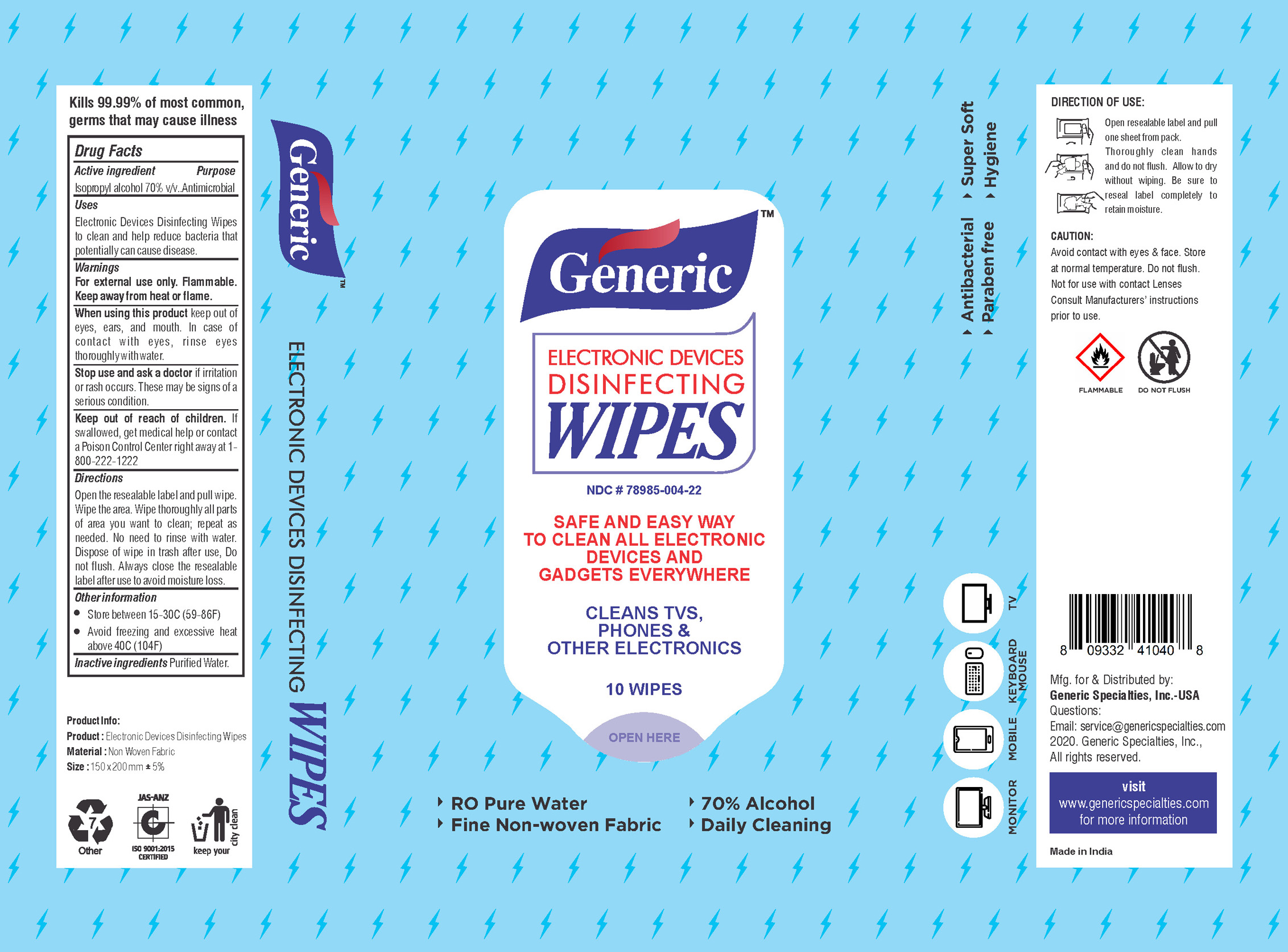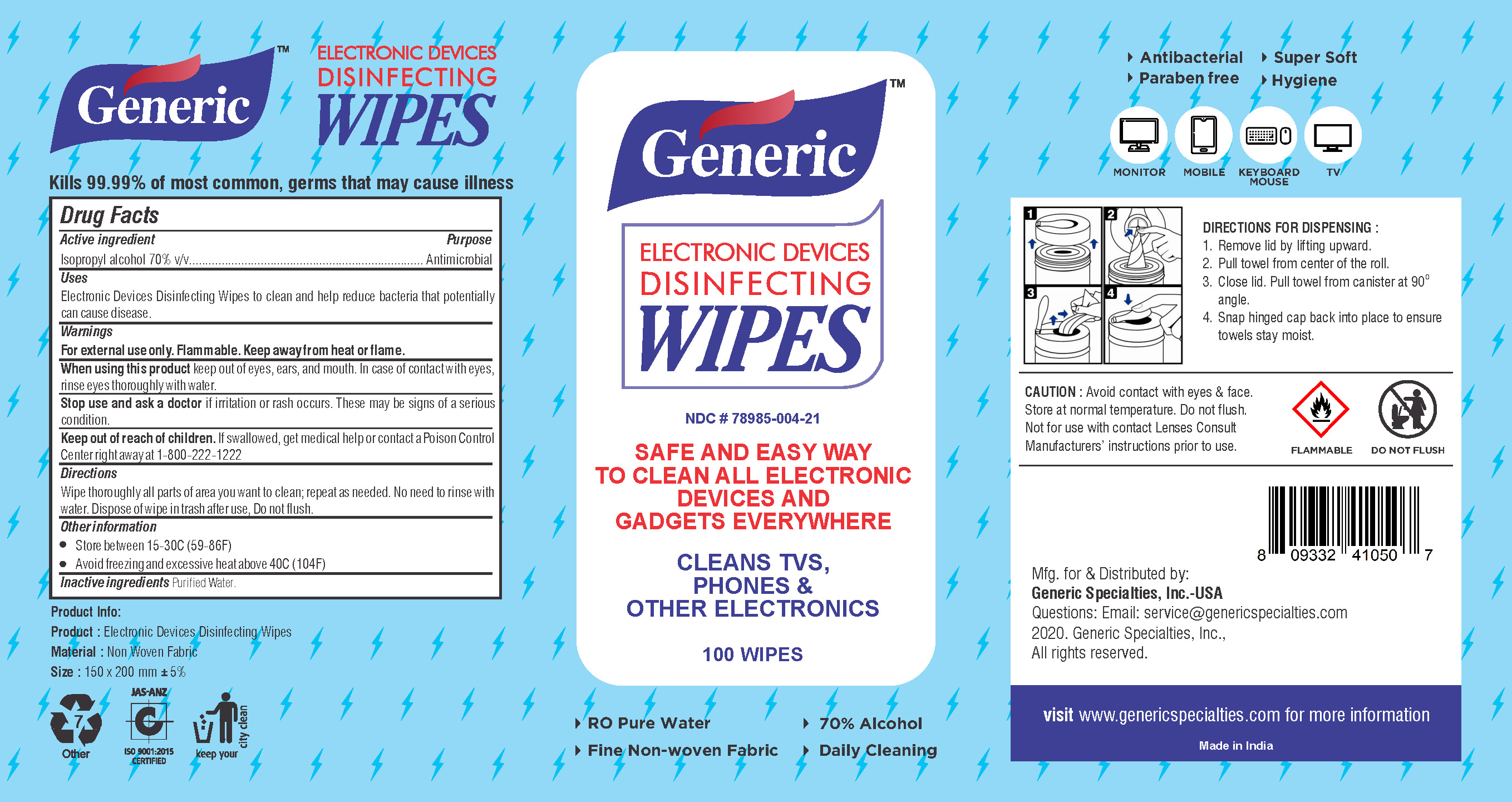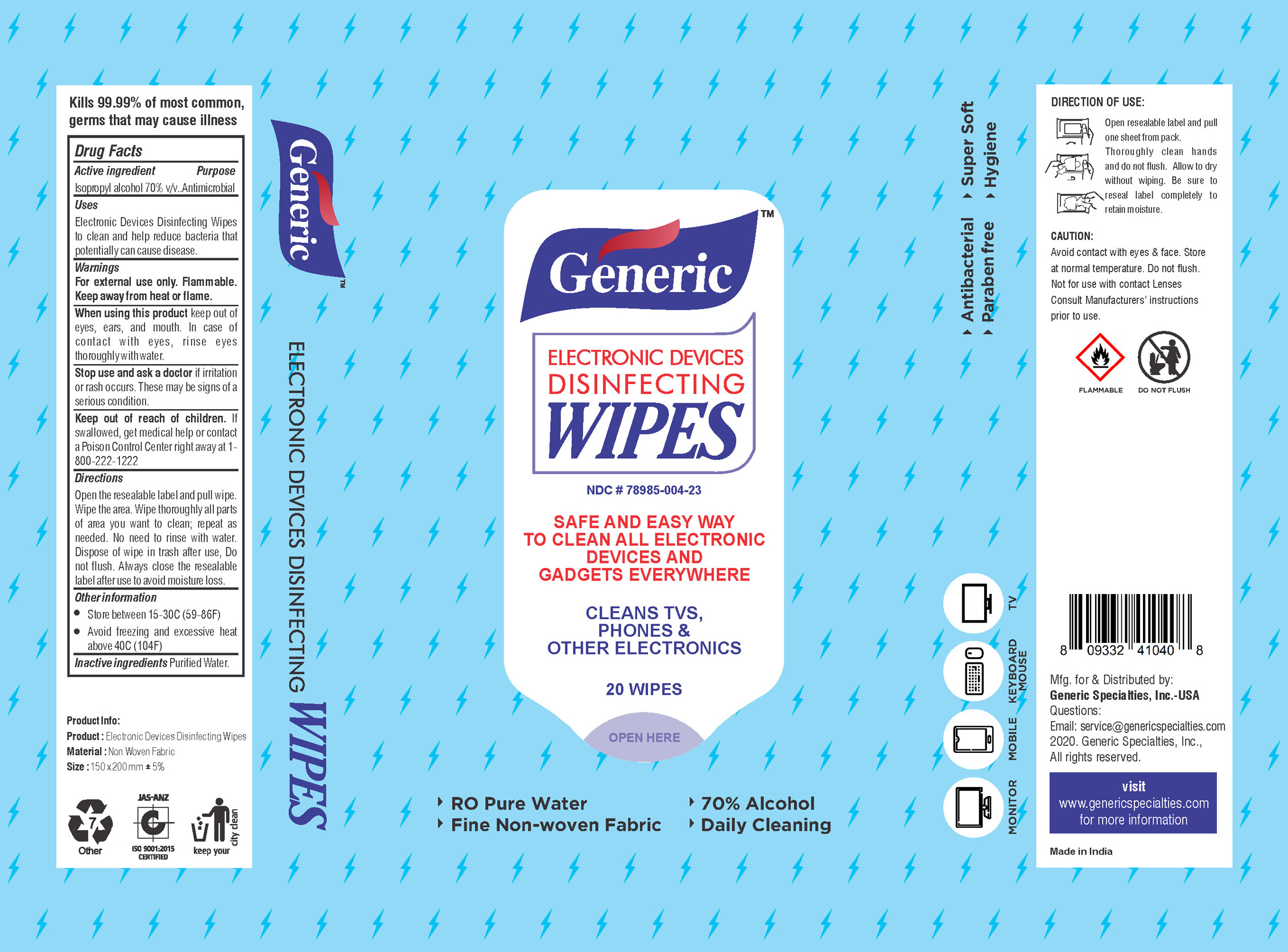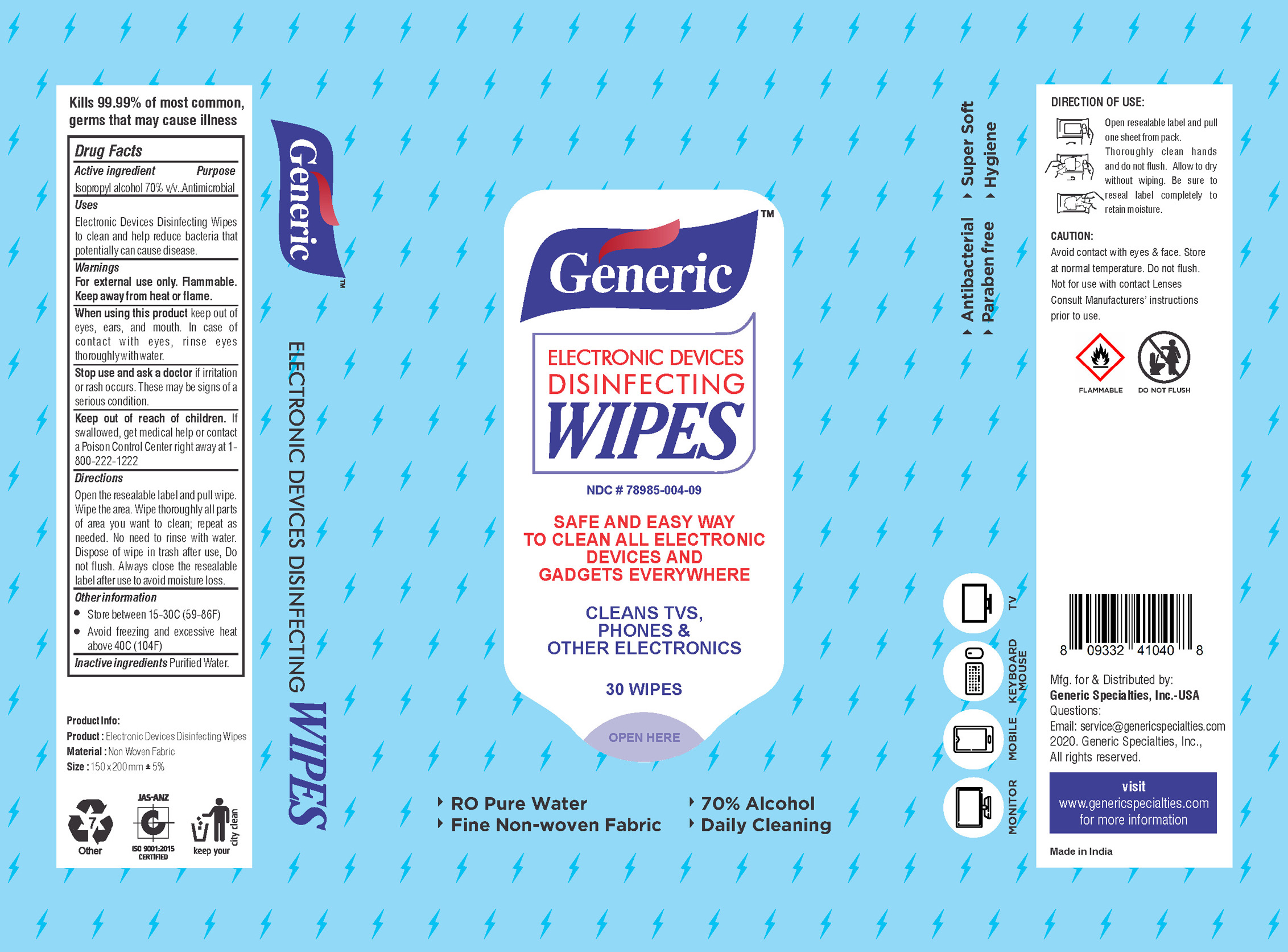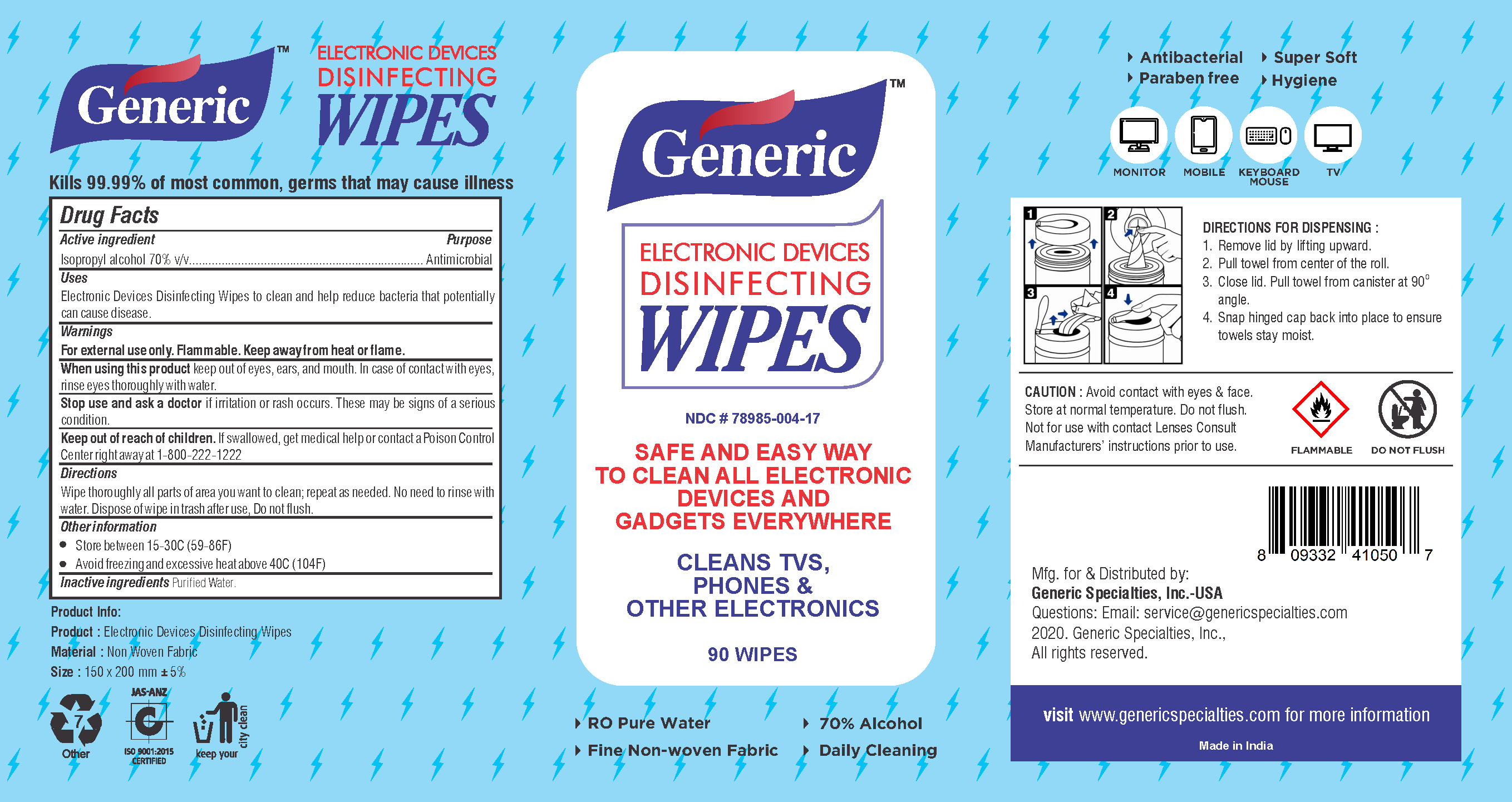 DRUG LABEL: Electronic Devices Disinfecting Wipes
NDC: 78985-004 | Form: SWAB
Manufacturer: Generic Specialties Inc.
Category: otc | Type: HUMAN OTC DRUG LABEL
Date: 20200928

ACTIVE INGREDIENTS: ISOPROPYL ALCOHOL 70 mL/100 1
INACTIVE INGREDIENTS: WATER

This is an Electronic Devices Disinfecting Wipes manufactured according to the Temporary Policy for Preparation of Certain Alcohol-Based Hand Sanitizer Products During the Public Health Emergency (CoViD-19); Guidance for Industry.

The hand sanitizing & moisturizing wipes are manufactured using only the following United States Pharmacopoeia (USP) grade ingredients in the preparation of the product (percentage in final product formulation) consistent with World Health Organization (WHO) recommendations:

Alcohol (Isopropyl alcohol) (USP or Food Chemical Codex (FCC) grade) (70%, volume/volume (v/v)) in an aqueous solution denatured according to Alcohol and Tobacco Tax and Trade Bureau regulations in 27 CFR part 20.

Purified water

The firm does not add other active or inactive ingredients. Different or additional ingredients may impact the quality and potency of the product

Active Ingredient(s)

Isopropyl Alcohol 70% v/v. Purpose: Antimicrobial

Purpose

Safe and easy way to clean electronics- Clean TVs, Phones & other Electronics.

Use

Electronic Devices Disinfecting Wipes to clean and help reduce bacteria that potentially cause disease.

Warnings

For external use only. Flammable. Keep away from heat or flame

Do not use

-

When using this product keep out of eyes, ears, and mouth. In case of contact with eyes, rinse eyes thoroughly with water.
Stop use and ask a doctor if irritation or rash occurs. These may be signs of a serious condition.
Keep out of reach of children. If swallowed, get medical help or contact a Poison Control Center right away.

Stop use and ask a doctor if irritation or rash occurs. These may be signs of a serious condition.

Keep out of reach of children. If swallowed, get medical help or contact a Poison Control Center right away at 1-800-222-1222

Directions

- Open the resealable label and pull wipe.Wipe the area. Wipe thoroughly all parts of area you want to clean, repeat as needed. No need to rinse with water. Dispose of wipe in trash after use. Do not flush. Always close the resealble label after use to avoid moisture loss.

Other information

- Store between 15-30C (59-86F)
- Avoid freezing and excessive heat above 40C (104F)

Inactive ingredients

Purified water

RECENT MAJOR CHANGES

Electronic Devices Disinfecting Wipes to clean and help reduce bacteria that potentially can cause disease.